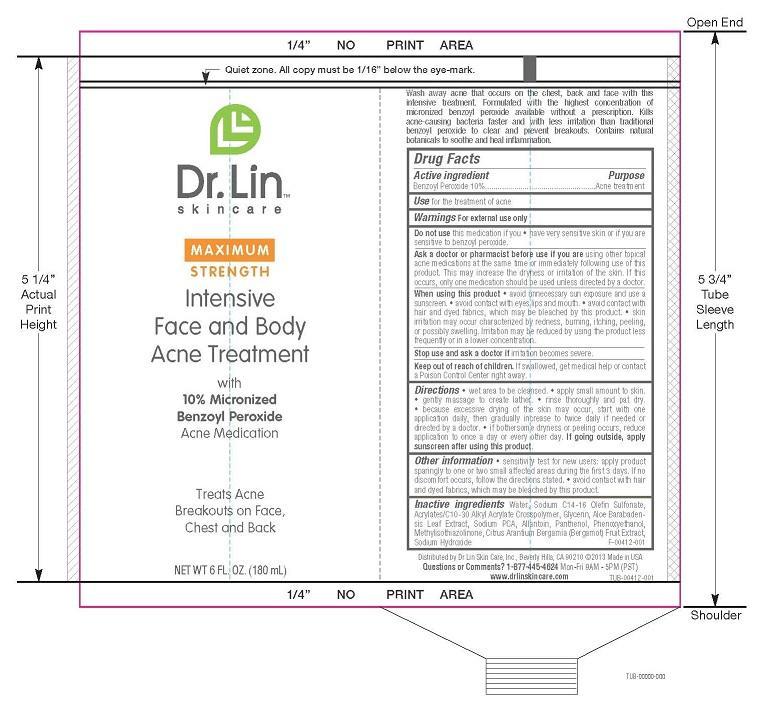 DRUG LABEL: INTENSIVE FACE AND BODY ACNE TREATMENT
NDC: 58876-107 | Form: GEL
Manufacturer: DR LIN SKINCARE
Category: otc | Type: HUMAN OTC DRUG LABEL
Date: 20140711

ACTIVE INGREDIENTS: BENZOYL PEROXIDE 10 g/100 mL
INACTIVE INGREDIENTS: WATER; SODIUM C14-16 OLEFIN SULFONATE; CARBOMER COPOLYMER TYPE A (ALLYL PENTAERYTHRITOL CROSSLINKED); GLYCERIN; ALOE VERA LEAF; SODIUM PYRROLIDONE CARBOXYLATE; ALLANTOIN; PANTHENOL; PHENOXYETHANOL; METHYLISOTHIAZOLINONE; BERGAMOT ORANGE; SODIUM HYDROXIDE

ACTIVE INGREDIENT

BENZYL PEROXIDE 10%

PURPOSE

ACNE TREATMENT

USE

FOR THE TREATMENT OF ACNE AND ACNE DARK AND RED MARKS.

WARNINGS

FOR EXTERNAL USE ONLY

DO NOT USE THIS MEDICATION IF YOU

- HAVE VERY SENSITIVE SKIN OR IF YOU ARE SENSITIVE TO BENZOYL PEROXIDE.

ASK A DOCTOR OR PHARMACIST BEFORE USE IF YOU ARE USING OTHER TOPICAL ACNE MEDICATIONS AT THE SAME TIME OR IMMEDIATELY FOLLOWING USE OF THIS PRODUCT. THIS MAY INCREASE DRYNESS OR IRRITATION OF THE SKIN. IF THIS OCCURS, ONLY ONE MEDICATION SHOULD BE USED UNLESS DIRECTED BY A DOCTOR.

When using this product

- avoid unnecessary sun exposure and use a sunscreen.
- avoid contact with eyes lips and mouth.
- avoid contact with hair and dyed fabrics, which may be bleached by this product.
- skin irritation may occur characterized by redness, burning, itching, peeling, or possibly swelling. Irritation may be reduced by using the product less frequently or in a lower concentration.

STOP USE AND ASK A DOCTOR IF IRRITATION BECOMES SEVERE.

KEEP OUT OF REACH OF CHILDREN. IF PRODUCT IS SWALLOWED, GET MEDICAL HELP OR CONTACT A POISON CONTROL CENTER RIGHT AWAY.

Directions

- wet area to be cleansed.
- apply small amount to skin.
- gently massage to create lather.
- rinse thoroughly and pat dry.
- because excessive drying of the skin may occur, start with one application daily, then gradually increase to twice daily if needed or directed by a doctor.
- if bothersome dryness or peeling occurs, reduce application to once a day or every other day. If going outside, apply sunscreen after using this product.

Other information

- sensitivity test for new users: apply product sparingly to one or two small affected areas during the first 3 days. If no discomfort occurs, follow the directions stated.
- avoid contact with hair and dyed fabrics, which may be bleached by this product.

INACTIVE INGREDIENTS

Water, Sodium C14-16 Olefin Sulfonate, Acrylates/C10-30 Alkyl Acrylate Crosspolymer, Glycerin, Aloe Barabadensis Leaf Extract, Sodium PCA, Allantoin, Panthenol, Phenoxyethanol, Methylisothiazolinone, Citrus Arantium Bergamia (Bergamot) Fruit Extract, Sodium Hydroxide

QUESTIONS OR COMMENTS?

1-877-445-4624

MON-FRI 8AM - 5PM (PST)